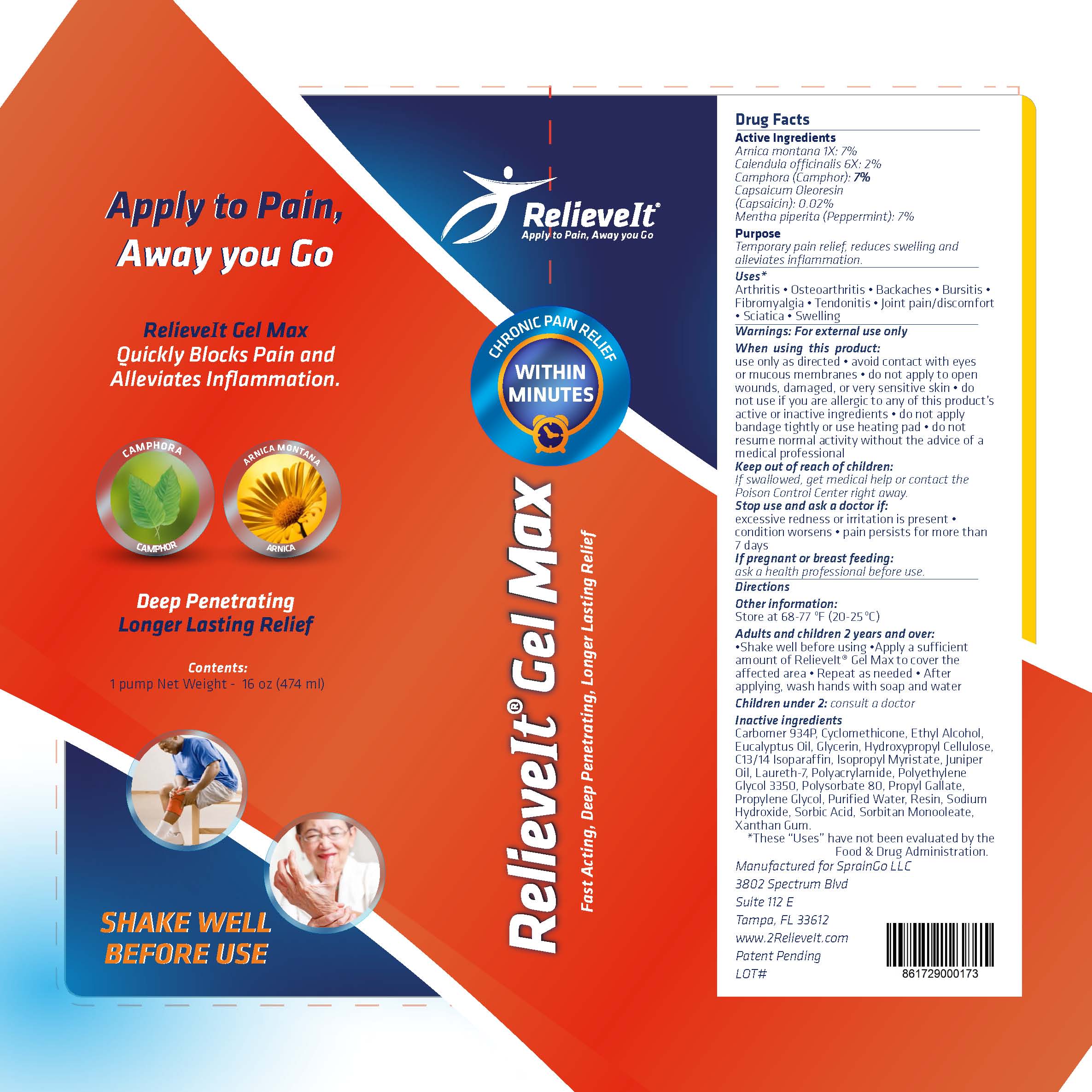 DRUG LABEL: RelieveIt Gel Max
NDC: 58133-953 | Form: GEL
Manufacturer: Cosmetic Specialty Labs, Inc.
Category: homeopathic | Type: HUMAN OTC DRUG LABEL
Date: 20181017

ACTIVE INGREDIENTS: CAMPHOR (NATURAL) 7 [hp_M]/1 mL; ARNICA MONTANA 7 [hp_M]/1 mL; MENTHA PIPERITA 7 [hp_M]/1 mL; CAPSAICIN 0.02 [hp_M]/1 mL; CALENDULA OFFICINALIS SEED OIL 2 [hp_M]/1 mL
INACTIVE INGREDIENTS: CYCLOMETHICONE; METHYL ALCOHOL; EUCALYPTUS OIL; LOW-SUBSTITUTED HYDROXYPROPYL CELLULOSE, UNSPECIFIED; JUNIPER BERRY OIL; POLYSORBATE 80; BENZOIN RESIN; SODIUM HYDROXIDE; PROPYLENE GLYCOL 2-METHYLBUTYRATE; POLYETHYLENE GLYCOL 3350; PROPYL GALLATE; GLYCERIN; ISOPROPYL MYRISTATE; POLYACRYLAMIDE (10000 MW); SORBIC ACID; XANTHAN GUM; WATER; AMMONIUM LAURETH-7 SULFATE; CARBOMER 934; SORBITAN MONOOLEATE; C13-14 ISOPARAFFIN

RelieveIt Gel Max

Active Ingredient

Arnica montana 1X: 7%

Calendula officinalis 6X: 2%

Camphora (Camphor): 7%

Capsaicum Oleoresin (Capsaicin): 0.02%

Mentha piperita (Peppermint): 7%)

Purpose

Temporary pain relief, reduces swelling and alleviates inflammation.

Uses:

Arthritis • Osteoarthritis • Backaches • Bursitis •

Fibromyalgia • Tendonitis • Joint pain/discomfort

• Sciatica • Swelling

Warnings:

for external use only

When using this product:

use only as directed • avoid contact with eyes

or mucous membranes • do not apply to open

wounds, damaged, or very sensitive skin • do

not use if you are allergic to any of this product’s

active or inactive ingredients • do not apply

bandage tightly or use heating pad • do not

resume normal activity without the advice of a

- medical professionall

Keep out of reach of children.

If swallowed, get medical help or contact the

Poison Control Center right away.

Directions:

Adults and children 2 years and over:

•Shake well before using •Apply a sufficient

amount of RelieveIt® Gel Max to cover the

affected area • Repeat as needed • After

applying, wash hands with soap and water

Children under 2: consult a doctor

Other ingredients:

Carbomer 934P, Cyclomethicone, Ethyl Alcohol,
Eucalyptus Oil, Glycerin, Hydroxypropyl Cellulose,
C13/14 Isoparaffin, Isopropyl Myristate, Juniper
Oil, Laureth-7, Polyacrylamide, Polyethylene
Glycol 3350, Polysorbate 80, Propyl Gallate,
Propylene Glycol, Purified Water, Resin, Sodium
Hydroxide, Sorbic Acid, Sorbitan Monooleate,
Xanthan Gum.
*These “Uses” have not been evaluated by the
Food & Drug Administration.

Stop use and ask a doctor if:

excessive redness or irritation is present •

condition worsens • pain persists for more than

7 days

If pregnant or breast feeding:

ask a health professional before use

Other Information

Store at 68-77°F (20-25°C)